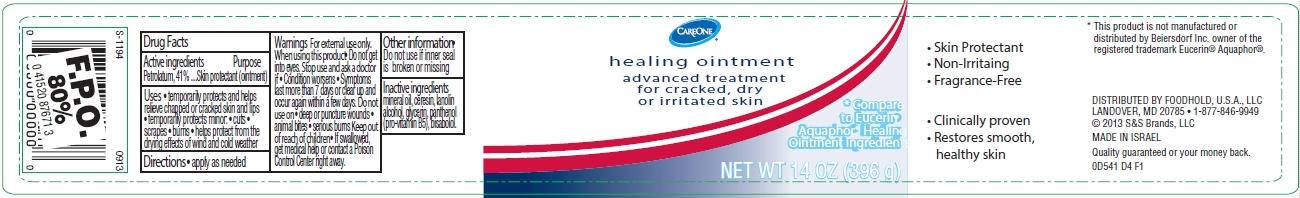 DRUG LABEL: CareOne Healing
NDC: 41520-541 | Form: OINTMENT
Manufacturer: American Sales Company
Category: otc | Type: HUMAN OTC DRUG LABEL
Date: 20130930

ACTIVE INGREDIENTS: PETROLATUM 41 g/100 g
INACTIVE INGREDIENTS: MINERAL OIL; CERESIN; LANOLIN; GLYCERIN; PANTHENOL; LEVOMENOL; ALCOHOL

CareOne Healing Ointment

Active ingredient

Petrolatum 41%

Purpose

Skin protectant (ointment)

Uses

- temporarily protects and helps relieve chapped or cracked skin and lips
- temporarily protects minor:
  cuts
  scrapes
  burns
- helps protect from the drying effects of wind and cold weather

Warnings

For external use only. When using this product

- Do not get into eyes. Stop use and ask a doctor if
  Condition worsens
  Symptoms last more than 7 days or clear up and occur again within a few days.
- Do not use on
  deep or puncture wounds
  animal bites
  serious burns
- Keep out of reach of children
- If swallowed, get medical help or contact a Poison Control Center right away.

Directions

Apply as needed

Other information

Do not use if inner seal is broken or missing

Inactive ingredients

mineral oil, ceresin, lanolin, alcohol, glycerin, panthenol (pro-viatmin B5), bisabolol.

Package/Label Principal Display Panel

CAREONE
healing ointment

advanced treatment for cracked, dry or irritated skin

*Compare to Eucerin® Aquaphor® Healing Ointment Ingredients

NET WT 14 OZ (396 g)

- Skin Protectant
- Non-Irritating
- Fragrance-Free
- Clinically proven
- Restores smooth, healthy skin

*This product is not manufactured or distributed by Beiersdorf Inc. owner of the registered trademark Eucerin® Aquaphor®.

DISTRIBUTED BY FOODHOLD, U.S.A., LLC
LANDOVER, MD 20785 1-877-846-9949
© 2013 S&S Brands, LLC

MADE IN ISRAEL

Quality guaranteed or your money back.

0D541 D4 F1

Jar Label